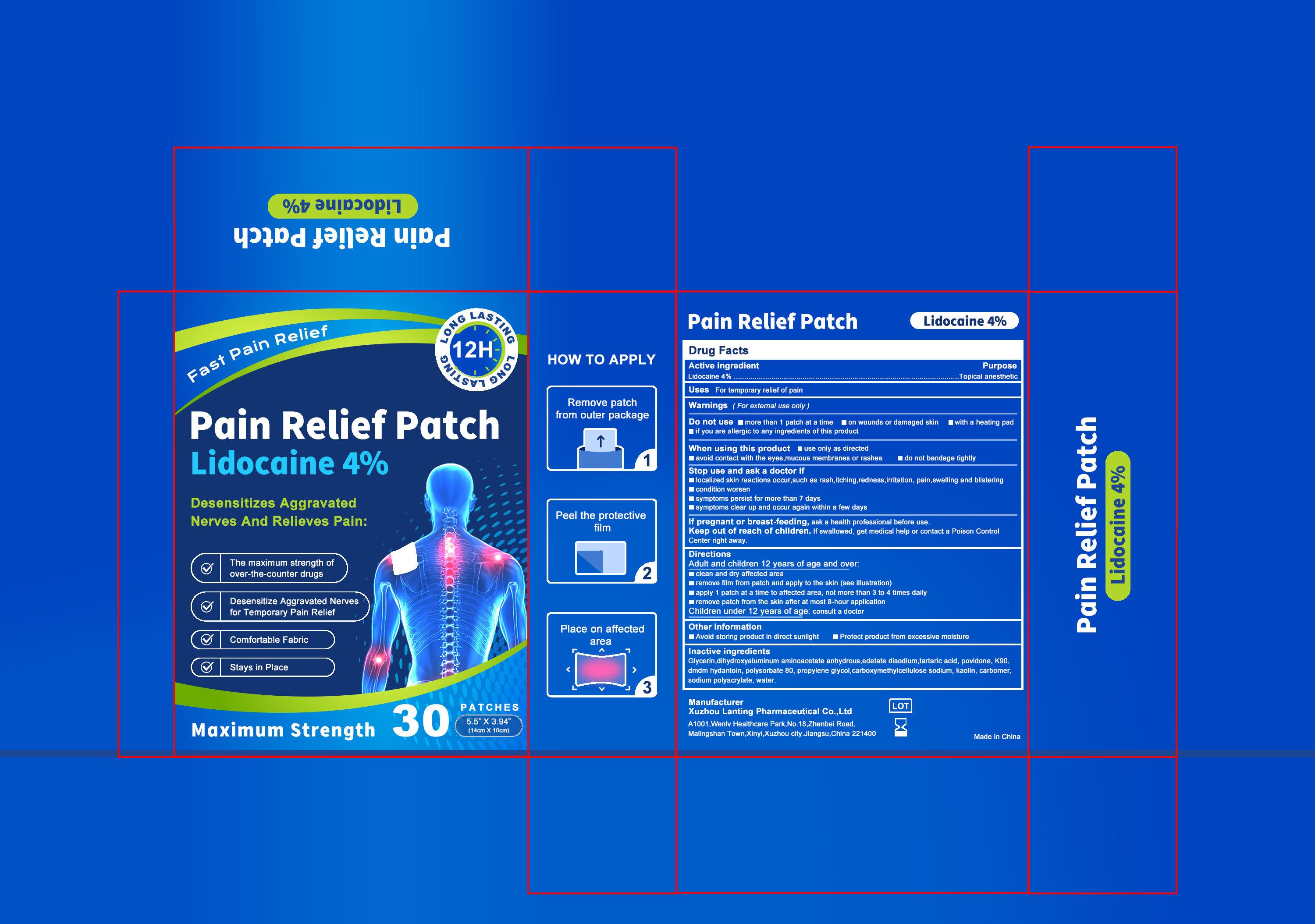 DRUG LABEL: 4% Lidocaine Pain Relief Patch
NDC: 87278-003 | Form: PATCH
Manufacturer: Guangxi Keyun E-commerce Co., Ltd.
Category: otc | Type: HUMAN OTC DRUG LABEL
Date: 20260129

ACTIVE INGREDIENTS: LIDOCAINE 0.04 g/1 1
INACTIVE INGREDIENTS: POLYSORBATE 80; WATER; EDETATE DISODIUM; KAOLIN; DIHYDROXYALUMINUM AMINOACETATE ANHYDROUS; CARBOMER; TARTARIC ACID; POVIDONE K90; GLYCERIN; PROPYLENE GLYCOL; SODIUM POLYACRYLATE (2500000 MW); DMDM HYDANTOIN; CARBOXYMETHYLCELLULOSE SODIUM

87278-003 4% Lidocaine Pain Relief Patch

ACTIVE INGREDIENT

Lidocaine 4%

PURPOSE

Topical anesthetic

INDICATIONS AND USAGE

For temporary relief of pain

WARNINGS

For external use only

DO NOT USE

more than 1 patch at a time
on wounds or damaged skin
with a heating pad
if you are allergic to any ingredients of this product

WHEN USING

use only as directed
avoid contact with the eyes,mucous membranes or rashes
do not bandage tightly

STOP USE

localized skin reactions occur,such as rash,itching,redness,irritation, pain,swelling and blistering
condition worsen
symptoms persist for more than 7 days
symptoms clear up and occur again within a few days

KEEP OUT OF REACH OF CHILDREN

If pregnant or breast-feeding, ask a health professional before use.
Keep out of reach of children. lf swallowed, get medical help or contact a Poison Control Center right away.

DOSAGE AND ADMINISTRATION

Adult and children 12 years of age and over:
clean and dry affected area
remove film from patch and apply to the skin (see illustration)
apply 1 patch at a time to affected area, not more than 3 to 4 times daily
remove patch from the skin after at most 8-hour application
Children under 12 years of age: consult a doctor

INACTIVE INGREDIENT

Glycerin
Dihydroxyaluminum aminoacetate anhydrous
Edetate disodium
Tartaric acid
Povidone K90
DMDM Hydantoin
Polysorbate 80
Propylene glycol
Carboxymethylcellulose sodium
Kaolin
Carbomer
Sodium polyacrylate
Water